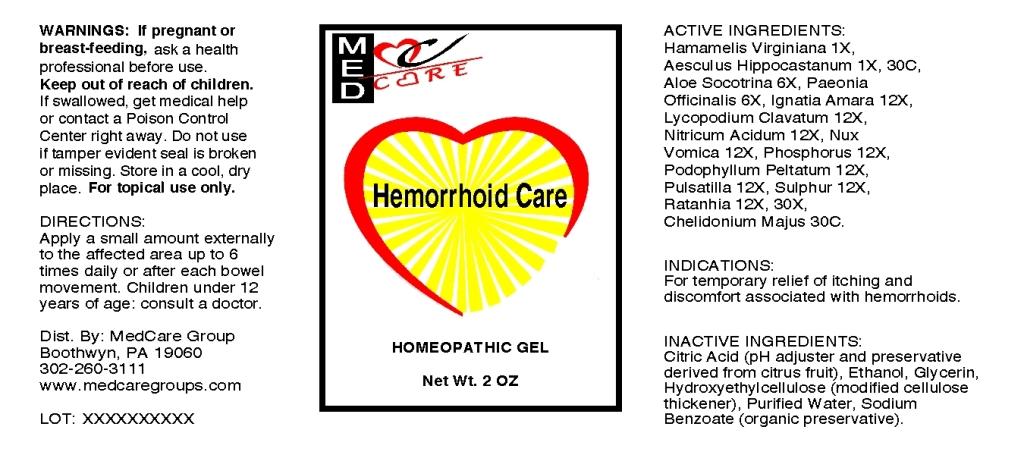 DRUG LABEL: Hemorrhoid Care
NDC: 57520-0778 | Form: GEL
Manufacturer: Apotheca Company
Category: homeopathic | Type: HUMAN OTC DRUG LABEL
Date: 20120126

ACTIVE INGREDIENTS: HAMAMELIS VIRGINIANA ROOT BARK/STEM BARK 1 [hp_X]/1 g; HORSE CHESTNUT 1 [hp_X]/1 g; ALOE 6 [hp_X]/1 g; PAEONIA OFFICINALIS ROOT 6 [hp_X]/1 g; STRYCHNOS IGNATII SEED 12 [hp_X]/1 g; LYCOPODIUM CLAVATUM SPORE 12 [hp_X]/1 g; NITRIC ACID 12 [hp_X]/1 g; STRYCHNOS NUX-VOMICA SEED 12 [hp_X]/1 g; PHOSPHORUS 12 [hp_X]/1 g; PODOPHYLLUM 12 [hp_X]/1 g; PULSATILLA VULGARIS 12 [hp_X]/1 g; SULFUR 12 [hp_X]/1 g; KRAMERIA LAPPACEA ROOT 12 [hp_X]/1 g; CHELIDONIUM MAJUS 30 [hp_C]/1 g
INACTIVE INGREDIENTS: CITRIC ACID MONOHYDRATE; ALCOHOL; GLYCERIN; WATER; SODIUM BENZOATE; CETYL HYDROXYETHYLCELLULOSE (350000 MW)

Hemorrhoid Care

ACTIVE INGREDIENT

ACTIVE INGREDIENTS: Hamamelis virginiana 1X, Aesculus hippocastanum 1X, 30C, Aloe socotrina 6X, Paeonia officinalis 6X, Ignatia amara 12X, Lycopodium clavatum 12X, Nitricum acidum 12X, Nux vomica 12X, Phosphorus 12X, Podophyllum peltatum 12X, Pulsatilla 12X, Sulphur 12X, Ratanhia 12X, 30X, Chelidonium majus 30C.

PURPOSE

INDICATIONS: For temporary relief of itching and discomfort associated with hemorrhoids.

WARNINGS

WARNINGS: If pregnant or breast-feeding, ask a health professional before use.

Keep out of reach of children. If swallowed, get medical help or contact a Poison Control Center right away.

Do not use if tamper evident seal is broken or missing.

Store in a cool, dry place

For topical use only.

DOSAGE AND ADMINISTRATION

DIRECTIONS: Apply a small amount externally to the affected area up to 6 times daily or after each bowel movement. Children under 12 years of age: Consult a doctor.

INACTIVE INGREDIENT

INACTIVE INGREDIENTS: Citric acid, Ethanol, Glycerin, Hydroxyethylcellulose, Purified water, Sodium benzoate.

KEEP OUT OF REACH OF CHILDREN. If swallowed, get medical help or contact a Poison Control Center right away.

INDICATIONS AND USAGE

INDICATIONS: For temporary relief of itching and discomfort associated with hemorrhoids.

QUESTIONS

Dist. By:

MedCare Group

Boothwyn, PA 19060

302-260-3111

www.medcaregroups.com

PACKAGE LABEL

MEDCARE

Hemorrhoid Care

HOMEOPATHIC GEL

Net. Wt. 2 OZ